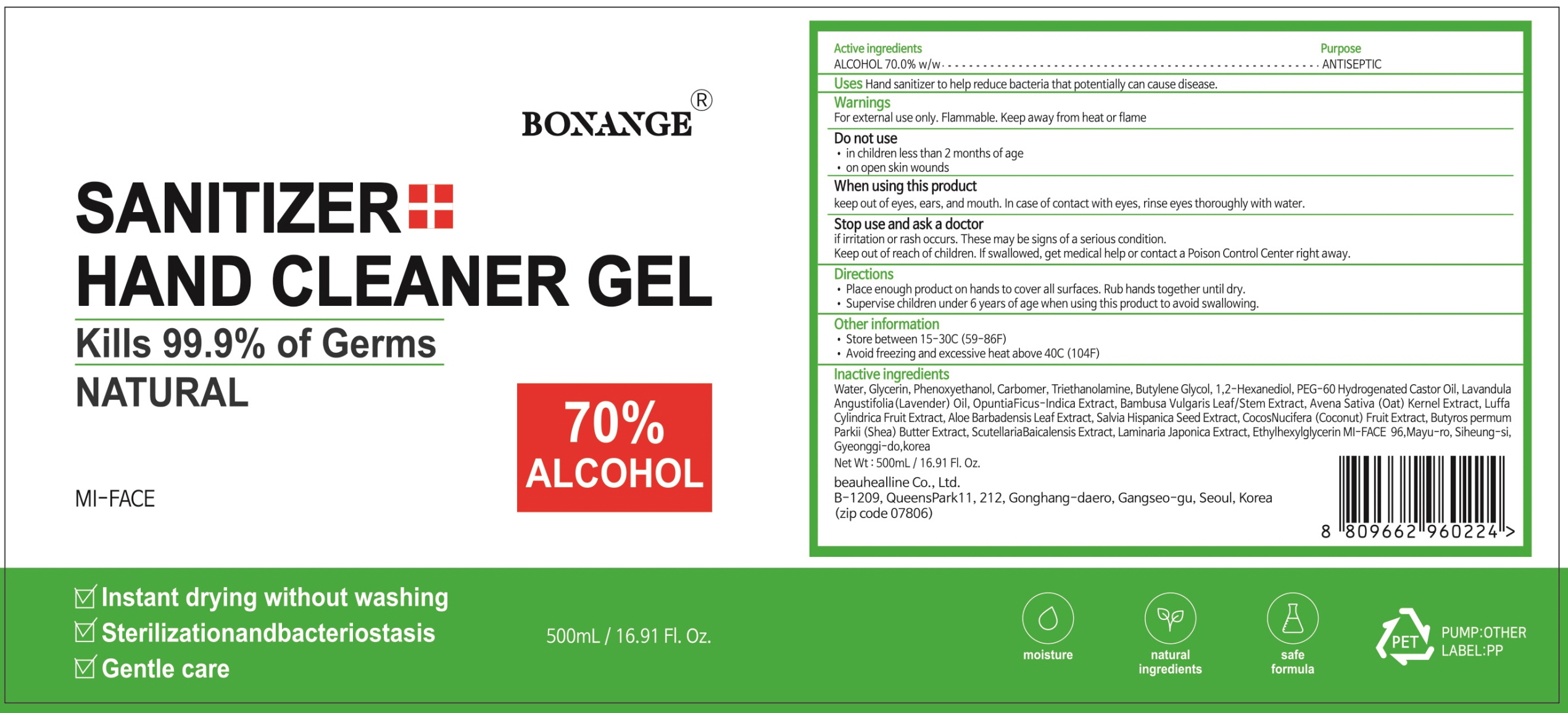 DRUG LABEL: BONANGE HAND CLEANER
NDC: 75005-010 | Form: GEL
Manufacturer: Mi-face Co., Ltd
Category: otc | Type: HUMAN OTC DRUG LABEL
Date: 20200831

ACTIVE INGREDIENTS: ALCOHOL 350.0 g/500 mL
INACTIVE INGREDIENTS: Water; GLYCERIN; Phenoxyethanol; CARBOMER HOMOPOLYMER, UNSPECIFIED TYPE; Trolamine; Butylene Glycol; 1,2-Hexanediol; PEG-60 Hydrogenated Castor Oil; LAVENDER OIL

Drug Facts

ACTIVE INGREDIENT

ALCOHOL 70.0% w/w

INACTIVE INGREDIENTS

Water, Glycerin, Phenoxyethanol, Carbomer, Triethanolamine, Butylene Glycol, 1,2-Hexanediol, PEG-60 Hydrogenated Castor Oil, Lavandula Angustifolia (Lavender) Oil, Opuntia Ficus-Indica Extract, Bambusa Vulgaris Leaf/Stem Extract, Avena Sativa (Oat) Kernel Extract, Luffa Cylindrica Fruit Extract, Aloe Barbadensis Leaf Extract, Salvia Hispanica Seed Extract, Cocos Nucifera (Coconut) Fruit Extract, Butyrospermum Parkii (Shea) Butter Extract, Scutellaria Baicalensis Extract, Laminaria Japonica Extract, Ethylhexylglycerin

PURPOSE

ANTISEPTIC

WARNINGS

For external use only. Flammable. Keep away from heat or flame
--------------------------------------------------------------------------------------------------------
Do not use
• in children less than 2 months of age
• on open skin wounds
--------------------------------------------------------------------------------------------------------
When using this product keep out of eyes, ears, and mouth. In case of contact with eyes, rinse eyes thoroughly with water.
--------------------------------------------------------------------------------------------------------
Stop use and ask a doctor if irritation or rash occurs. These may be signs of a serious condition.

Keep out of reach of children. If swallowed, get medical help or contact a Poison Control Center right away.

Uses

■ Hand sanitizer to help reduce bacteria that potentially can cause disease.

Directions

• Place enough product on hands to cover all surfaces. Rub hands together until dry.

• Supervise children under 6 years of age when using this product to avoid swallowing.

Other Information

• Store between 15-30C (59-86F)
• Avoid freezing and excessive heat above 40C (104F)